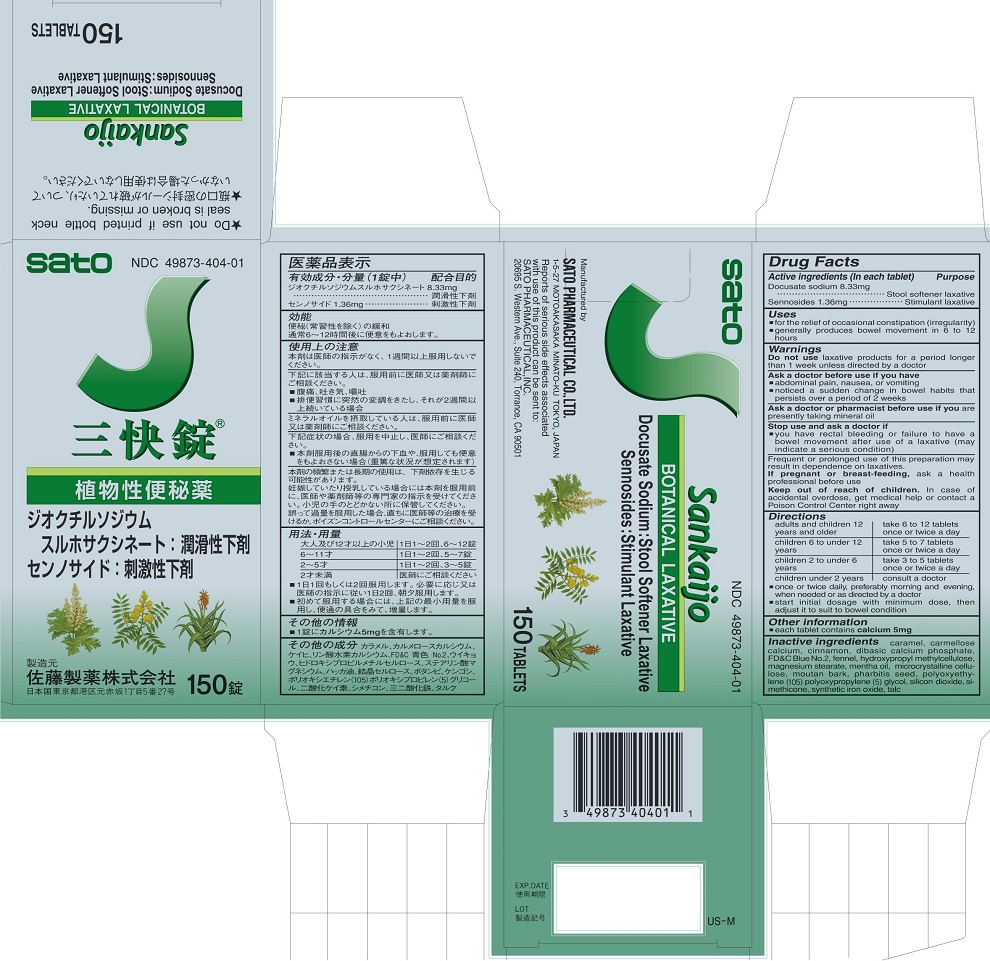 DRUG LABEL: Sankaijo
NDC: 49873-404 | Form: TABLET
Manufacturer: Sato Pharmaceutical Co., Ltd.
Category: otc | Type: HUMAN OTC DRUG LABEL
Date: 20231129

ACTIVE INGREDIENTS: DOCUSATE SODIUM 8.33 mg/1 1; SENNOSIDES 1.36 mg/1 1
INACTIVE INGREDIENTS: CELLULOSE, MICROCRYSTALLINE; PAEONIA SUFFRUTICOSA ROOT BARK; IPOMOEA NIL SEED; PEG/PPG-105/5 COPOLYMER; SILICON DIOXIDE; DIMETHICONE; FERRIC OXIDE RED; TALC; CARAMEL; CARBOXYMETHYLCELLULOSE CALCIUM; CALCIUM PHOSPHATE, DIBASIC, ANHYDROUS; FD&C BLUE NO. 2; FENNEL; HYPROMELLOSE 2910 (15000 MPA.S); MAGNESIUM STEARATE

Sankaijo

Active ingredients (in each tablet)
Docusate sodium 8.33mg
Sennosides 1.36mg

Purposes
Docusate sodium Stool softener laxative
Sennosides Stimulant laxative

Uses
■for the relief of occasional constipation (irregularity)
■generally produces bowel movement in 6 to 12 hours

Warnings

Do not use laxative products for a period longer than 1 week unless directed by a doctor

Ask a doctor before use if you have
■abdominal pain, nausea, or vomiting
■noticed a sudden change in bowel habits that persists over a period of 2 weeks

Ask a doctor or pharmacist before useif you are presently taking mineral oil

Stop use and ask a doctor if
■you have rectal bleeding or failure to have a bowel movement after use of a laxative (may indicate a serious condition)

PREGNANCY OR BREAST FEEDING

If pregnant or breast-feeding, ask a health professional before use.

Keep out of reach of children. In case of accidental overdose, get medical help or contact a Poison Control Center right away.

GENERAL PRECAUTIONS

Frequent or prolonged use of this preparation may result in dependence on laxatives.

Directions
adults and children 12 years and older - take 6 to 12 tablets once or twice a day
children 6 to under 12 years - take 5 to 7 tablets once or twice a day
children 2 to under 6 years - take 3 to 5 tablets once or twice a day
children under 2 years - consult a doctor
■once or twice daily, preferably morning and evening, when needed or as directed by a doctor
■start initial dosage with minimum dose, then adjust it to suit to bowel condition

Other information
■each tablet contains calcium 5 mg

INACTIVE INGREDIENT

Inactive ingredients caramel, carmellose calcium, cinnamon, dibasic calcium phosphate, FDandC Blue No. 2, fennel, hydroxypropyl methylcellulose, magnesium stearate, mentha oil, microcrystalline cellulose, moutan bark, pharbitis seed, polyoxyethylene (105) polyoxypropylene (5) glycol, silicon dioxide, simethicone, synthetic iron oxide, talc